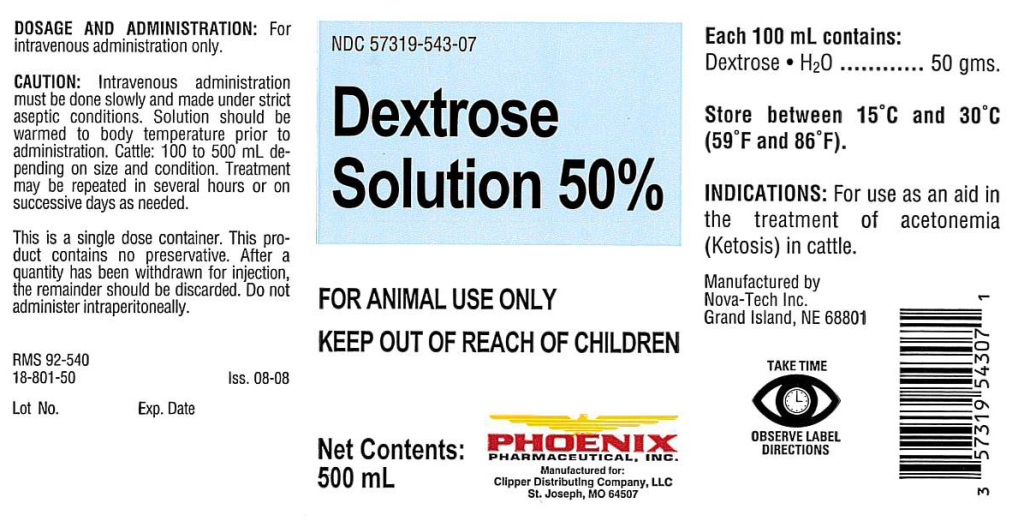 DRUG LABEL: Dextrose
NDC: 57319-543 | Form: INJECTION, SOLUTION
Manufacturer: Clipper
Category: animal | Type: OTC ANIMAL DRUG LABEL
Date: 20170814

ACTIVE INGREDIENTS: DEXTROSE MONOHYDRATE 50 g/100 mL

Dextrose Solution 50%

DOSAGE AND ADMINISTRATION:

For
intravenous administration only.

CAUTION:

Intravenous administration
must be done slowly and made under strict
aseptic conditions. Solution should be
warmed to body temperature prior to
administration. Cattle: 100 to 500 mL de-
pending on size and condition. Treatment
may be repeated in several hours or on
successive days as needed.

This is a single dose container. This pro-
duct contains no preservative. After a
quantity has been withdrawn for injection,
the remainder should be discarded. Do not
administer intraperitoneally.

GENERAL PRECAUTIONS

FOR ANIMAL USE ONLY
KEEP OUT OF REACH OF CHILDREN

Each 100 mL contains:

Dextrose • H2O..............50 gms.

STORAGE AND HANDLING

Store between 15°C and 30°C
(59°F and 86°F).

INDICATIONS:

For use as an aid in
the treatment of acetonemia
(Ketosis) in cattle.

GENERAL PRECAUTIONS

TAKE TIME OBSERVE LABEL DIRECTIONS

INFORMATION FOR OWNERS/CAREGIVERS

RMS 92-540

18-801-50

Iss. 08-08

Lot No.

Exp. Date

Net Contents:
500 mL

Manufactured for:
Clipper Distributing Company, LLC
St. Joseph, MO 64507

Manufactured by
Nova-Tech Inc.
Grand Island, NE 68801